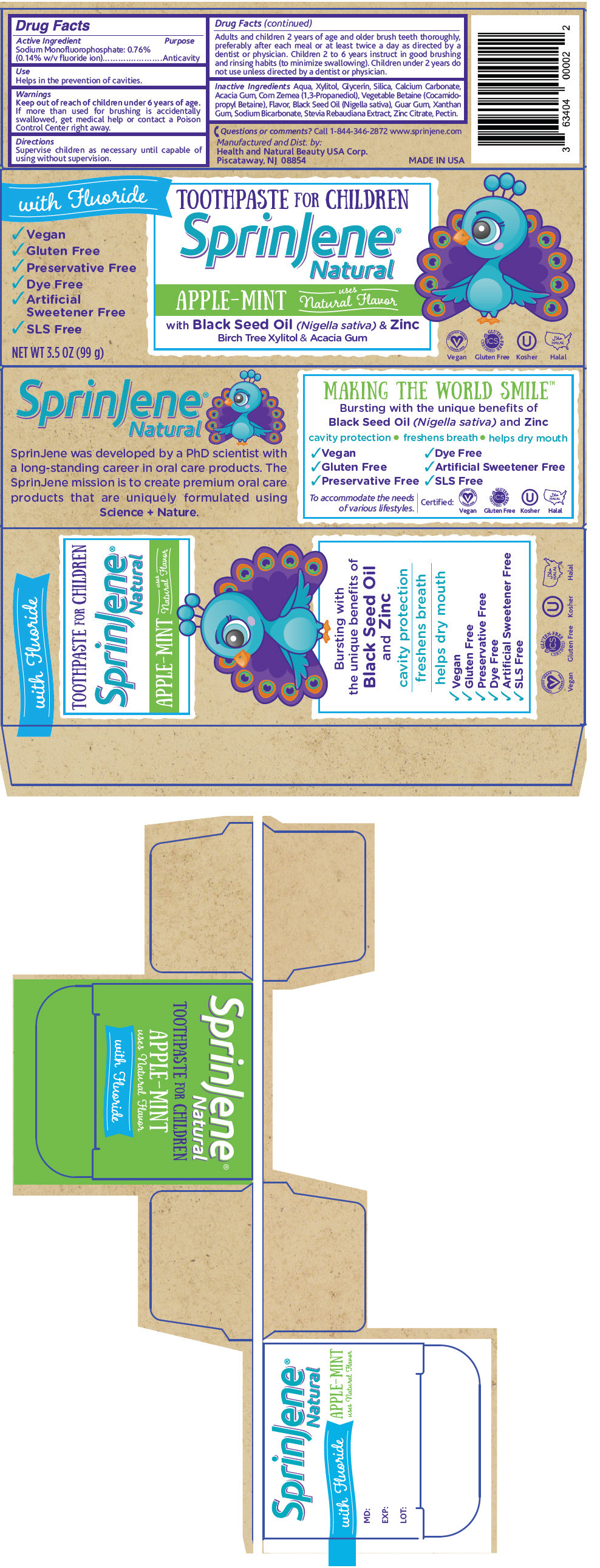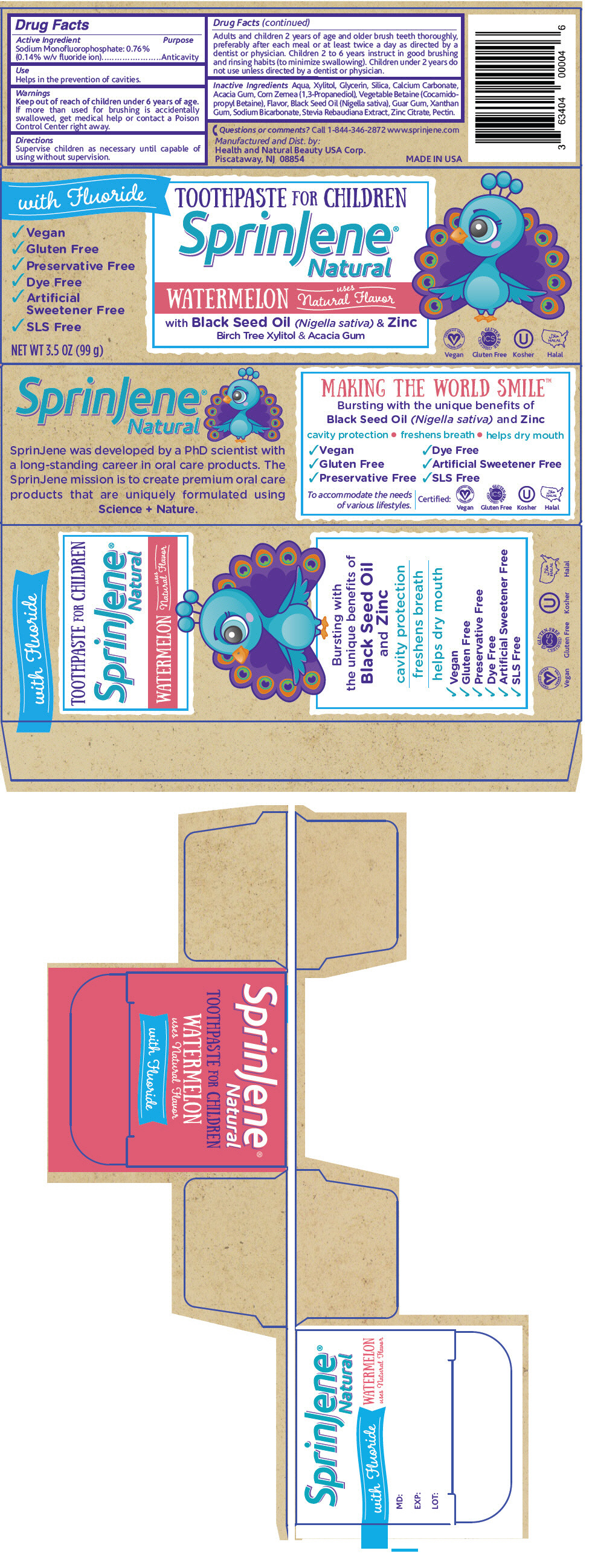 DRUG LABEL: SprinJene 
NDC: 63404-2014 | Form: PASTE, DENTIFRICE
Manufacturer: Health and Natural Beauty USA Corp
Category: otc | Type: HUMAN OTC DRUG LABEL
Date: 20170117

ACTIVE INGREDIENTS: Sodium Monofluorophosphate 1.5 mg/1 g
INACTIVE INGREDIENTS: WATER; Xylitol; Glycerin; Silicon Dioxide; Calcium Carbonate; Acacia; Cocamidopropyl Betaine; Guar Gum; Xanthan Gum; Sodium Bicarbonate; Zinc Citrate; Pectin

SprinJene®

Drug Facts

Active Ingredient

Sodium Monofluorophosphate: 0.76% (0.14% w/v fluoride ion)

Purpose

Anticavity

Use

Helps in the prevention of cavities.

Warnings

Keep out of reach of children under 6 years of age.

If more than used for brushing is accidentally swallowed, get medical help or contact a Poison Control Center right away.

Directions

Supervise children as necessary until capable of using without supervision.

Adults and children 2 years of age and older brush teeth thoroughly, preferably after each meal or at least twice a day as directed by a dentist or physician. Children 2 to 6 years instruct in good brushing and rinsing habits (to minimize swallowing). Children under 2 years do not use unless directed by a dentist or physician.

Inactive Ingredients

Aqua, Xylitol, Glycerin, Silica, Calcium Carbonate, Acacia Gum, Corn Zemea (1,3-Propanediol), Vegetable Betaine (Cocamidopropyl Betaine), Flavor, Black Seed Oil (Nigella sativa), Guar Gum, Xanthan Gum, Sodium Bicarbonate, Stevia Rebaudiana Extract, Zinc Citrate, Pectin.

Questions or comments?

Call 1-844-346-2872 www.sprinjene.com

Manufactured and Dist. by:
Health and Natural Beauty USA Corp.
Piscataway, NJ 08854

PRINCIPAL DISPLAY PANEL - 99 g Tube Carton - Natural Apple-Mint

with Fluoride
TOOTHPASTE FOR CHILDREN

✓ Vegan
✓ Gluten Free
✓ Preservative Free
✓ Dye Free
✓ Artificial
  Sweetener Free
✓ SLS Free

SprinJene®
Natural

APPLE-MINT
uses
Natural Flavor

with Black Seed Oil (Nigella sativa) & Zinc
Birch Tree Xylitol & Acacia Gum

NET WT 3.5 OZ (99 g)

CERTIFIED VEGAN
VEGAN.ORG
Vegan

GLUTEN-FREE
CERTIFIED
Gluten Free

U
Kosher

HALAL
Halal

PRINCIPAL DISPLAY PANEL - 99 g Tube Carton - Natural Watermelon

with Fluoride
TOOTHPASTE FOR CHILDREN

✓ Vegan
✓ Gluten Free
✓ Preservative Free
✓ Dye Free
✓ Artificial
  Sweetener Free
✓ SLS Free

SprinJene®
Natural

WATERMELON
uses
Natural Flavor

with Black Seed Oil (Nigella sativa) & Zinc
Birch Tree Xylitol & Acacia Gum

NET WT 3.5 OZ (99 g)

CERTIFIED VEGAN
VEGAN.ORG
Vegan

GLUTEN-FREE
CERTIFIED
Gluten Free

U
Kosher

HALAL
Halal